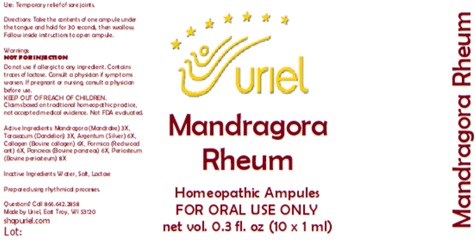 DRUG LABEL: Mandragora Rheum
NDC: 48951-7015 | Form: LIQUID
Manufacturer: Uriel Pharmacy Inc.
Category: homeopathic | Type: HUMAN OTC DRUG LABEL
Date: 20260227

ACTIVE INGREDIENTS: MANDRAGORA OFFICINARUM ROOT 3 [hp_X]/1 mL; TARAXACUM PALUSTRE ROOT 3 [hp_X]/1 mL; SILVER 6 [hp_X]/1 mL; BOVINE TYPE I COLLAGEN 6 [hp_X]/1 mL; FORMICA RUFA 6 [hp_X]/1 mL; SUS SCROFA PANCREAS 6 [hp_X]/1 mL; BOS TAURUS BONE 8 [hp_X]/1 mL
INACTIVE INGREDIENTS: WATER; SODIUM CHLORIDE; LACTOSE

Mandragora Rheum

PURPOSE

Use: Temporary relief of sore joints.

INDICATIONS AND USAGE

FOR ORAL USE ONLY

DOSAGE AND ADMINISTRATION

Directions: Take the contents of one ampule under the tongue and hold for 30 seconds, then swallow. Follow inside instructions to open ampule.

Warnings:
NOT FOR INJECTION
Do not use if allergic to any ingredient. Contains traces of lactose. Consult a physician if symptoms worsen. If pregnant or nursing, consult a physician before use.
Claims based on traditional homeopathic practice, not accepted medical evidence. Not FDA evaluated

KEEP OUT OF REACH OF CHILDREN.

ACTIVE INGREDIENT

Active Ingredients: Mandragora (Mandrake) 3X, Taraxacum (Dandelion) 3X, Argentum (Silver) 6X, Collagen (Bovine collagen) 6X, Formica (Red wood ant) 6X, Pancreas (Bovine pancreas) 6X, Periosteum (Bovine periosteum) 8X

Inactive Ingredients: Water, Salt, Lactose

QUESTIONS

Questions? Call 866.642.2858 Made by Uriel, East Troy, WI 53120 shopuriel.com